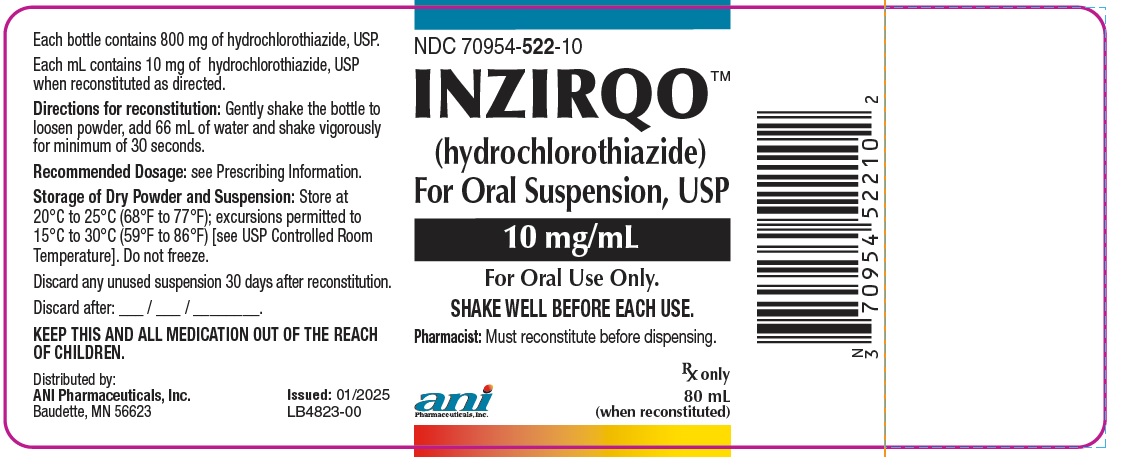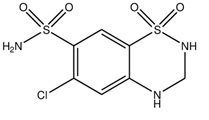 DRUG LABEL: INZIRQO
NDC: 70954-522 | Form: POWDER, FOR SUSPENSION
Manufacturer: ANI Pharmaceuticals, Inc.
Category: prescription | Type: Human Prescription Drug Label
Date: 20251216

ACTIVE INGREDIENTS: HYDROCHLOROTHIAZIDE 10 mg/1 mL
INACTIVE INGREDIENTS: SUCROSE; ANHYDROUS CITRIC ACID; POTASSIUM SORBATE; POWDERED CELLULOSE; XANTHAN GUM; TALC; MALTODEXTRIN; PROPYLENE GLYCOL; SODIUM CHLORIDE; CARAMEL; MOLASSES; ACACIA

HIGHLIGHTS OF PRESCRIBING INFORMATION

These highlights do not include all the information needed to use INZIRQO safely and effectively. See full prescribing information for INZIRQO.
INZIRQO (hydrochlorothiazide), for oral suspension
Initial U.S. Approval: 1959

1 INDICATIONS & USAGE

INZIRQO™ (hydrochlorothiazide) is a thiazide diuretic indicated for:

- The treatment of hypertension in adult and pediatric patients alone or in combination with other antihypertensive agents, to lower blood pressure. Lowering blood pressure reduces the risk of fatal and nonfatal cardiovascular events, primarily strokes and myocardial infarction (1.1).
- The treatment of edema associated with congestive heart failure, hepatic cirrhosis and renal disease including the nephrotic syndrome in adult and pediatric patients. (1.2).

2 DOSAGE & ADMINISTRATION

- For the treatment of hypertension in adults: The recommended initial dose in adults is 25 mg orally daily given as a single dose. As needed, increase the dose to 50 mg orally daily, given as a single or two divided doses(2.1).
- For the treatment of edema in adults: The recommended adult dosage is 25 mg to 100 mg orally daily as a single or divided dose. Consider intermittent therapy to reduce the risk of electrolyte imbalances, i.e., administration on alternate days or on 3 to 5 days each week (2.2).
- For the treatment of hypertension and edema in pediatric patients: The recommended pediatric dosage is 1 mg/kg to 2 mg/kg orally per day in single or two divided doses. Do not exceed 37.5 mg per day in patients less than 2 years of age or 100 mg per day in children 2 to less than 13 years of age. Patients less than 6 months of age may require doses up to 3 mg/kg orally per day in two divided doses (2.1, 2.2).

3 DOSAGE FORMS & STRENGTHS

For oral suspension: 10 mg/mL (3)

4 CONTRAINDICATIONS

- Anuria (4)
- Hypersensitivity to hydrochlorothiazide or any ingredient in INZIRQO (4)
- Hypersensitivity to sulfonamide-derived drugs (4)

5 WARNINGS AND PRECAUTIONS

- Monitor kidney function periodically (5.1)
- Monitor and correct serum electrolytes prior to use and monitor periodically (5.2).
- Monitor blood sugar, lipid levels, uric acid and calcium levels periodically. (5.3)
- Exacerbation or activation of systemic lupus erythematosus (5.4)
- Acute angle-closure glaucoma and acute myopia (5.5)

6 ADVERSE REACTIONS

Adverse reactions include hypokalemia, hyponatremia, hypomagnesemia, hyperglycemia, hyperuricemia, hyperlipidemia and hypotension. See Adverse Reactions (6)

To report SUSPECTED ADVERSE REACTIONS, contact ANI Pharmaceuticals, Inc. at 1-855-204-1431 or FDA at 1-800-FDA-1088 or www.fda.gov/medwatch.

7 DRUG INTERACTIONS

- NSAID: May lead to increased risk of renal impairment and loss of diuretic and antihypertensive effect (7.1).
- Cholestyramine and colestipol: Reduced absorption of thiazides (7.1)
- Lithium: Increased lithium concentrations and lithium toxicity (7.2)
- Antidiabetic drugs: Dosage adjustment of antidiabetic may be required (7.2)

FULL PRESCRIBING INFORMATION

1 INDICATIONS & USAGE

1.1 Hypertension

INZIRQO is indicated for the treatment of hypertension in adult and pediatric patients, to lower blood pressure.

Lowering blood pressure reduces the risk of fatal and non-fatal cardiovascular events, primarily strokes and myocardial infarctions. These benefits have been seen in controlled trials of antihypertensive drugs from a wide variety of pharmacologic classes., including the class to which this drug principally belongs.

Control of high blood pressure should be part of comprehensive cardiovascular risk management including, as appropriate, lipid control, diabetes management, antithrombotic therapy, smoking cessation, exercise, and limited sodium intake. Many patients will require more than one drug to achieve blood pressure goals. For specific advice on goals and management, see published guidelines, such as those of the National High Blood Pressure Education Program’s Joint National Committee on Prevention, Detection, Evaluation, and Treatment of High Blood Pressure (JNC).

Numerous antihypertensive drugs, from a variety of pharmacologic classes and with different mechanisms of action have been shown in randomized controlled trials to reduce cardiovascular morbidity and mortality, and it can be concluded that it is blood pressure reduction, and not some other pharmacologic property of the drugs, that is largely responsible for those benefits. The largest and most consistent cardiovascular outcome benefit has been a reduction in the risk of stroke, but reductions in myocardial infarction and cardiovascular mortality also have been seen regularly.

Elevated systolic or diastolic pressure causes increased cardiovascular risk, and the absolute risk increase per mmHg is greater at higher blood pressures, so that even modest reductions of severe hypertension can provide substantial benefit. Relative risk reduction from blood pressure reduction is similar across populations with varying absolute risk, so the absolute benefit is greater in patients who are at higher risk independent of their hypertension (for example, patients with diabetes or hyperlipidemia), and such patients would be expected to benefit from more aggressive treatment to a lower blood pressure goal.

Some antihypertensive drugs have smaller blood pressure effects (as monotherapy) in black patients, and many antihypertensive drugs have additional approved indications and effects (e.g., on angina, heart failure, or diabetic kidney disease). These considerations may guide selection of therapy.

INZIRQO can be used alone or in combination with other antihypertensive agents.

1.2 Edema

Treatment of edema associated with congestive heart failure, hepatic cirrhosis, and renal disease including the nephrotic syndrome in adult and pediatric patients.

2 DOSAGE & ADMINISTRATION

2.1 Recommended Dosage for the Treatment of Hypertension

The recommended initial dose in adults is 25 mg orally daily given as a single dose. As needed, increase the dose to 50 mg orally daily, given as a single or two divided doses.

Pediatric Patients:

The recommended dose in pediatric patients is 1 to 2 mg/kg per day in one or two divided doses not to exceed 37.5 mg in patients less than 2 years of age and 100 mg in patients 2 to less than 13 years of age. In pediatric patients less than 6 months of age, doses up to 3 mg/kg per day in two divided doses may be required.

2.2 Recommended Dosage for the Treatment of Edema

The recommended adult dosage is 25 mg to 100 mg orally daily as a single or divided dose. Consider intermittent therapy to reduce the risk of electrolyte imbalances, i.e., administration on alternate days or on 3 to 5 days each week.

Pediatric Patients:

The recommended dose in pediatric patients is 1 to 2 mg/kg per day in one or two divided doses not to exceed 37.5 mg in patients less than 2 years of age and 100 mg in patients 2 to less than 13 years of age. In pediatric patients less than 6 months of age, doses up to 3 mg/kg per day in two divided doses may be required.

2.3 Preparation of Oral Suspension

INZIRQO is supplied as a powder for oral suspension and must be reconstituted prior to dispensing.

- Gently shake the bottle to loosen the powder, add 66 mL of water and shake vigorously for minimum of 30 seconds. When reconstituted as directed, the solution will result in a 10 mg/mL concentration of hydrochlorothiazide.
- Store the reconstituted solution at 20°C to 25°C (68°F to 77°F); excursions permitted to 15°C to 30°C (59°F to 86°F) [see USP Controlled Room Temperature]. Do not freeze.
- Write the date of expiration of the reconstituted oral suspension (calculated as 30 days after reconstitution) on the bottle label.

2.4 Important Administration Instructions

- Instruct patients or caregivers to use an oral dosing syringe to correctly measure the prescribed amount of medication. Inform patients that a bottle adapter and oral dosing syringes may be obtained from their pharmacy.
- Advise patients to always shake the bottle well prior to each use.
- INZIRQO may be administered with or without food [see Clinical Pharmacology (12.3)].

3 DOSAGE FORMS & STRENGTHS

For Oral Suspension: When reconstituted as directed, INZIRQO is an off-white to light brown colored suspension with caramel, peppermint flavor containing 10 mg/mL of hydrochlorothiazide, USP.

4 CONTRAINDICATIONS

INZIRQO is contraindicated:

- In patients with anuria.
- In patients with hypersensitivity to hydrochlorothiazide or any ingredient in INZIRQO.
- In patients with hypersensitivity to sulfonamide-derived drugs.

5 WARNINGS AND PRECAUTIONS

5.1 Impaired Renal Function

Monitor kidney function periodically. Diuretics can cause hypovolemia which may precipitate acute kidney injury. Patients with chronic kidney disease, heart failure, or volume depletion may be at particular risk of developing acute renal failure on INZIRQO. Consider withholding or discontinuing therapy in patients who develop a clinically significant decrease in kidney function while on INZIRQO.

5.2 Electrolyte Abnormalities

INZIRQO can cause potentially symptomatic hypokalemia, hyponatremia, hypomagnesemia, and hypochloremic alkalosis. Hypomagnesemia can result in hypokalemia which appears difficult to treat despite potassium repletion. Hypokalemia is dose dependent. Monitor and correct serum electrolytes prior to use and monitor periodically. Discontinue INZIRQO if hypokalemia is associated with clinical symptoms (e.g., ECG changes, muscular weakness).

5.3 Metabolic Disturbances

INZIRQO may increase blood sugar levels, affect diabetes control, and cause changes in the need for diabetes medication.

INZIRQO may raise serum levels of cholesterol and triglycerides. Monitor blood sugar and lipid levels.

INZIRQO may raise the serum uric acid level due to reduced clearance of uric acid and may cause or exacerbate hyperuricemia and precipitate gout in susceptible patients. Increases in serum uric acid are dose related.

INZIRQO decreases urinary calcium excretion and may cause elevations of serum calcium. Monitor calcium levels in patients with hypercalcemia receiving INZIRQO.

Discontinue thiazides before carrying out tests for parathyroid function.

5.4 Systemic Lupus Erythematosus

Thiazide diuretics have been reported to cause exacerbation or activation of systemic lupus erythematosus.

5.5 Acute Angle-Closure Glaucoma and Acute Myopia

Hydrochlorothiazide, a sulfonamide, can cause an idiosyncratic reaction resulting in acute angle closure glaucoma and elevated intraocular pressure with or without a noticeable acute myopic shift and/or choroidal effusions. Symptoms include acute onset of decreased visual acuity or ocular pain and typically occur within hours to weeks of drug initiation. Untreated acute angle-closure glaucoma may result in permanent vision loss. Discontinue drug intake. Consider prompt medical or surgical treatments if the intraocular pressure remains uncontrolled. Risk factors for developing acute angle-closure glaucoma may include a history of sulfonamide or penicillin allergy.

6 ADVERSE REACTIONS

The following adverse reactions with INZIRQO are described elsewhere:

- Impaired Renal Function [see Warnings and Precautions (5.1)]
- Electrolyte Abnormalities [see Warnings and Precautions (5.2)]
- Metabolic Disturbances [see Warnings and Precautions (5.3)]
- Systemic Lupus Erythematosus [see Warnings and Precautions (5.4)]
- Acute Angle-Closure Glaucoma and Acute Myopia [see Warnings and Precautions (5.5)]

6.1 Clinical Trials Experience

The following adverse reactions have been reported and, within each category, are listed in order of decreasing severity.

Body as a Whole: Weakness.

Cardiovascular: Hypotension including orthostatic hypotension (may be aggravated by alcohol, barbiturates, narcotics or antihypertensive drugs).

Gastrointestinal: Pancreatitis, jaundice (intrahepatic cholestatic jaundice), diarrhea, vomiting, sialadenitis, cramping, constipation, gastric irritation, nausea, anorexia.

Hematologic: Aplastic anemia, agranulocytosis, leukopenia, hemolytic anemia, thrombocytopenia.

Hypersensitivity: Anaphylactic reactions, necrotizing angiitis (vasculitis and cutaneous vasculitis), respiratory distress including pneumonitis and pulmonary edema, photosensitivity, fever, urticaria, rash, purpura.

Metabolic: Electrolyte imbalance, hyperglycemia, glycosuria, hyperuricemia.

Musculoskeletal: Muscle spasm.

Nervous System: Vertigo, paresthesia, dizziness, headache, restlessness.

Renal: Renal failure, renal dysfunction, interstitial nephritis.

Skin and Appendages: Erythema multiforme including Stevens-Johnson syndrome, exfoliative dermatitis including toxic epidermal necrolysis, alopecia.

Special Senses: Transient blurred vision, xanthopsia.

Urogenital System: Impotence.

6.2 Postmarketing Experience

The following adverse reactions have been identified during postapproval use of hydrochlorothiazide.

Non-melanoma Skin Cancer

Hydrochlorothiazide is associated with an increased risk of non-melanoma skin cancer. In a study conducted in the Sentinel System, increased risk was predominantly for squamous cell carcinoma (SCC) and in white patients taking large cumulative doses. The increased risk for SCC in the overall population was approximately 1 additional case per 16,000 patients per year, and for white patients taking a cumulative dose of ≥ 50,000 mg the risk increase was approximately 1 additional SCC case for every 6,700 patients per year.

7 DRUG INTERACTIONS

7.1 Potential for Other Drugs to Affect INZIRQO

- Non-Steroidal Anti-Inflammatory Agents:Administration of a nonsteroidal anti-inflammatory agent, including a selective COX-2 inhibitor can reduce the diuretic, natriuretic, and antihypertensive effects of thiazide diuretics. Therefore, when INZIRQO and nonsteroidal anti-inflammatory agents are used concomitantly, check to determine if the desired effect of the diuretic is obtained.
- Cholestyramine and Colestipol: Absorption of hydrochlorothiazide is impaired in the presence of anionic exchange resins. Stagger the dosage of INZIRQO and the resin such that INZIRQO is administered at least 4 hours before or 4 to 6 hours after the administration of the resin.

7.2 Potential for INZIRQO to Affect Other Drugs

- Lithium: Increases in serum lithium concentrations and lithium toxicity have been reported during concomitant administration of hydrochlorothiazide. Monitor serum lithium levels during concomitant use and adjust the lithium dose during concomitant administration or discontinuation of hydrochlorothiazide.
- Antidiabetic Drugs (oral agents and insulin): Dosage adjustment of the antidiabetic drug may be required when coadministered with hydrochlorothiazide.

8 USE IN SPECIFIC POPULATIONS

8.1 Pregnancy

Risk Summary

Untreated hypertension during pregnancy can lead to adverse outcomes for the mother and the fetus (see Clinical Considerations). Available data from published observational studies have not demonstrated a drug-associated risk of major birth defects, miscarriage or adverse maternal outcomes with hydrochlorothiazide use during pregnancy. However, there have been rare reports of jaundice, thrombocytopenia, and electrolyte imbalances in infants exposed to thiazide medications during pregnancy.

The background risk of major birth defects and miscarriage for the indicated population is unknown. In the U.S. general population, the estimated background risk of major birth defects and miscarriage in clinically recognized pregnancies is 2 to 4% and 15 to 20%, respectively.

Clinical Considerations

Disease-associated maternal and/or embryo/fetal risk

Hypertension in pregnancy increases the maternal risk for pre-eclampsia, gestational diabetes, premature delivery, and delivery complications (e.g., need for cesarean section, and post-partum hemorrhage). Hypertension increases the fetal risk for intrauterine growth restriction and intrauterine death. Monitor pregnant women with hypertension.

Data

Animal Data

Teratogenic effects: Studies in which hydrochlorothiazide was orally administered to pregnant mice and rats during their respective periods of major organogenesis at doses up to 3000 and 1000 mg hydrochlorothiazide /kg (approximately 146-fold and 97-fold the maximum recommended human dose based on body surface area), respectively, provided no evidence of harm to the fetus.

8.2 Lactation

Risk Summary

Available data from published literature indicate hydrochlorothiazide is present in human milk (see Data). There are no reports of adverse effects on breastfed infants exposed to hydrochlorothiazide during lactation. Doses of hydrochlorothiazide associated with clinically significant diuresis have been associated with impaired milk production. Consider the developmental and health benefits of breastfeeding along with the mother’s clinical need for INZIRQO and any potential adverse effects on the breastfed infant from INZIRQO or from the underlying maternal condition.

Data

A single study involving one woman and her infant showed a peak concentration of 275 mcg/L at 3 hours following 50 mg dose. No drug was detected (<20 mcg/L) in the infant’s plasma at 2 and 11 hours following the mother’s dose.

8.4 Pediatric Use

INZIRQO is approved for use in pediatric patients for the following:

- Treatment of hypertension to lower blood pressure
- Treatment of edema associated with congestive heart failure, hepatic cirrhosis, and renal disease, including the nephrotic syndrome

8.5 Hepatic Impairment

Monitor for mental status changes when using INZIRQO in patients with hepatic impairment because fluid shifts may precipitate hepatic coma.

10 OVERDOSAGE

The most common signs and symptoms observed are those caused by electrolyte depletion (hypokalemia, hypochloremia, hyponatremia) and dehydration resulting from excessive diuresis.

The degree to which hydrochlorothiazide is removed by hemodialysis has not been established.

11 DESCRIPTION

Hydrochlorothiazide, USP is a diuretic and antihypertensive. It is the 3,4-dihydro derivative of chlorothiazide. It is chemically designated as 6-chloro-3,4-dihydro-2 H-1,2,4-benzothiadiazine-7-sulfonamide 1,1-dioxide and has the following structural formula:

Hydrochlorothiazide, USP is a white, or practically white, crystalline powder which is slightly soluble in water, freely soluble in sodium hydroxide solution, in n-butylamine, and in dimethylformamide; sparingly soluble in methanol; insoluble in ether, in chloroform, and in dilute mineral acids. The molecular formula is C7H8ClN3O4S2 and the molecular weight is 297.74.

INZIRQO (hydrochlorothiazide) is supplied in one strength as an off-white to light-brown colored powder for oral suspension. When reconstituted with 66 mL of water, the total volume of the suspension is 80 mL containing 10 mg/mL of hydrochlorothiazide, USP. In addition, INZIRQO contains the following inactive ingredients: anhydrous citric acid, caramel flavor (artificial flavor, caramel, maltodextrin, molasses, propylene glycol, salt and sucrose), cellulose, peppermint flavor (acacia and natural flavor), potassium sorbate, sucrose, talc and xanthan gum.

12 CLINICAL PHARMACOLOGY

12.1 Mechanism of Action

Thiazides affect the renal tubular mechanisms of electrolyte reabsorption, directly increasing excretion of sodium and chloride in approximately equivalent amounts. Indirectly, the diuretic action of hydrochlorothiazide reduces plasma volume, with consequent increases in plasma renin activity, increases in aldosterone secretion, increases in urinary potassium loss, and decreases in serum potassium.

The mechanism of the antihypertensive effect of thiazides is not fully understood.

12.2 Pharmacodynamics

Hydrochlorothiazide does not usually affect normal blood pressure. Hydrochlorothiazide affects the distal renal tubular mechanism of electrolyte reabsorption. At maximal therapeutic dosage, all thiazides are approximately equal in their diuretic efficacy. Hydrochlorothiazide increases excretion of sodium and chloride in approximately equivalent amounts. Natriuresis may be accompanied by some loss of potassium and bicarbonate. After oral use, diuresis begins within 2 hours, peaks in about 4 hours and lasts about 6 to 12 hours.

12.3 Pharmacokinetics

Over a dose range of 50 to 100 mg, peak plasma hydrochlorothiazide concentrations and exposure (AUC) of INZIRQO increases proportionally with dose in healthy subjects.

Absorption

Following single-dose oral administration of 100 mg INZIRQO to healthy subjects in the fasted state, the AUC and Cmax of hydrochlorothiazide was 5940 ng.h/mL and 972 ng/mL, respectively. The peak plasma hydrochlorothiazide concentrations are achieved at approximately 1.5 hours.

Effect of Food: A food-effect study involving administration of INZIRQO to healthy male and female subjects after a high-fat, high calorie breakfast indicated that the rate of absorption (Cmax) decreased 38%, while the extent of absorption (AUC) remained unchanged, when compared to administration under fasting conditions. The Tmax was delayed by 2 hours.

Cholestyramine and Colestipol Resins: Absorption of hydrochlorothiazide is impaired in the presence of anionic exchange resins. Single doses of either cholestyramine or colestipol resins reduced the bioavailability of hydrochlorothiazide by up to 85% and 43%, respectively.

Distribution

Hydrochlorothiazide binds to albumin (40% to 70%) and distributes into erythrocytes. It crosses the placental but not the blood-brain barrier and is excreted in breast milk.

Elimination

Following oral administration of INZIRQO, plasma hydrochlorothiazide concentrations decline biexponentially, with a terminal elimination half-life of about 10 hours. At least 61% of the oral dose is eliminated unchanged in the urine within 24 hours.

13 NONCLINICAL TOXICOLOGY

13.1 Carcinogenesis & Mutagenesis & Impairment Of Fertility

Two year feeding studies in mice and rats conducted under the auspices of the National Toxicology Program (NTP) uncovered no evidence of a carcinogenic potential of hydrochlorothiazide in female mice (at doses of up to approximately 600 mg/kg/day) or in male and female rats (at doses of up to approximately 100 mg/kg/day). The NTP, however, found equivocal evidence for hepatocarcinogenicity in male mice.

Hydrochlorothiazide was not genotoxic in vitro in the Ames mutagenicity assay of Salmonella typhimurium strains TA 98, TA 100, TA 1535, TA 1537, and TA 1538 and in the Chinese Hamster Ovary (CHO) test for chromosomal aberrations, or in vivo in assays using mouse germinal cell chromosomes, Chinese hamster bone marrow chromosomes, and the Drosophila sex-linked recessive lethal trait gene. Positive test results were obtained only in the in vitro CHO Sister Chromatid Exchange (clastogenicity)and in the Mouse Lymphoma Cell (mutagenicity) assays, using concentrations of hydrochlorothiazide from 43 to 1300 mcg/mL, and in the Aspergillus nidulans nondisjunction assay at an unspecified concentration.

16 HOW SUPPLIED/STORAGE AND HANDLING

16.1 How Supplied

INZIRQO (hydrochlorothiazide) is supplied as an off-white to light-brown colored powder for oral suspension in one strength containing 800 mg of hydrochlorothiazide, USP in a HDPE bottle.

When reconstituted as directed, INZIRQO forms an off-white to light brown colored suspension with caramel, peppermint flavor. The total volume of the suspension is 80 mL containing 10 mg of hydrochlorothiazide, USP per mL (70954-522-10).

16.2 Storage

Store at 20°C to 25°C (68°F to 77°F); excursions permitted to 15°C to 30°C (59°F to 86°F) [see USP Controlled Room Temperature]. Do not freeze.

Keep this and all medication out of the reach of children.

Store reconstituted solutions of INZIRQO at 20°C to 25°C (68°F to 77°F); excursions permitted to 15°C to 30°C (59°F to 86°F) [see USP Controlled Room Temperature]. [see Dosage and Administration (2.3)].

17 PATIENT COUNSELING INFORMATION

Acute Angle-Closure Glaucoma and Acute Myopia

Advise patients to discontinue INZIRQO and seek immediate medical attention if they experience symptoms of Acute Myopia or Secondary Angle-Closure Glaucoma [see Warnings and Precautions (5.5)].

Non-melanoma Skin Cancer

Instruct patients taking hydrochlorothiazide to protect skin from the sun and undergo regular skin cancer screening [see Postmarketing Experience (6.2)].

Recommended Administration

Advise patients to always shake the bottle well before each use and measure the dose using a calibrated oral dosing syringe to ensure that the dose is measured and administered accurately. Inform patients that a bottle adapter and oral dosing syringes may be obtained from their pharmacy.

Advise patients never to use household teaspoons or tablespoons to measure INZIRQO.

Advise patients that the oral suspension should be stored at room temperature (20°C to 25°C (68°F to 77°F); excursions permitted to 15°C to 30°C (59°F to 86°F)).

INZIRQO may be taken with or without meals.

Discard any unused suspension 30 days after reconstitution.

Trademarks are the property of their respective owners.

Distributed by:

ANI Pharmaceuticals, Inc.,

Baudette, MN 56623

LB4824-01

INZIRQO is a pending trademark of ANI Pharmaceuticals, Inc.

PACKAGE LABEL.PRINCIPAL DISPLAY PANEL

INZIRQO (hydrochlorothiazide) Powder for Oral Suspension, 10 mg/mL

NDC 70954-522-10 - 80 mL (when reconstituted)